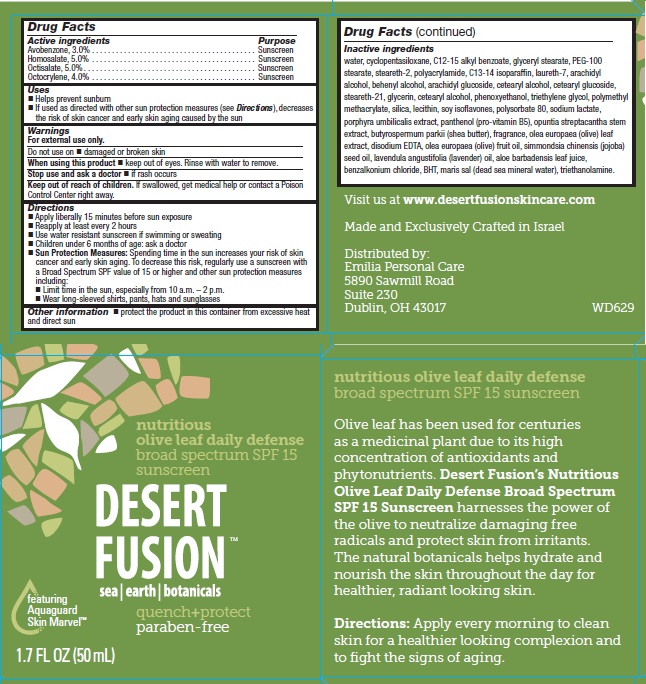 DRUG LABEL: Desert Fusion Nutritious Olive Leaf Daily Defense Broad Spectrum SPF 15 Sunscreen
NDC: 42421-692 | Form: CREAM
Manufacturer: Emilia Personal Care Inc.
Category: otc | Type: HUMAN OTC DRUG LABEL
Date: 20141208

ACTIVE INGREDIENTS: AVOBENZONE 3 g/100 g; HOMOSALATE 5 g/100 g; OCTISALATE 5 g/100 g; OCTOCRYLENE 4 g/100 g
INACTIVE INGREDIENTS: WATER; CYCLOMETHICONE 5; ALKYL (C12-15) BENZOATE; GLYCERYL MONOSTEARATE; PEG-100 STEARATE; STEARETH-2; C13-14 ISOPARAFFIN; LAURETH-7; ARACHIDYL ALCOHOL; DOCOSANOL; ARACHIDYL GLUCOSIDE; CETOSTEARYL ALCOHOL; CETEARYL GLUCOSIDE; STEARETH-21; GLYCERIN; PHENOXYETHANOL; TRIETHYLENE GLYCOL; POLY(METHYL METHACRYLATE; 450000 MW); SILICON DIOXIDE; SOY ISOFLAVONES; POLYSORBATE 80; SODIUM LACTATE; PORPHYRA UMBILICALIS; PANTHENOL; OPUNTIA STREPTACANTHA STEM; SHEA BUTTER; OLEA EUROPAEA LEAF; EDETATE DISODIUM; OLIVE OIL; JOJOBA OIL; LAVENDER OIL; ALOE VERA LEAF; BENZALKONIUM CHLORIDE; BUTYLATED HYDROXYTOLUENE; TROLAMINE

Desert Fusion Nutritious Olive Leaf Daily Defense
Broad Spectrum SPF 15 Sunscreen

Active ingredients

Avobenzone, 3.0%

Homosalate, 5.0%

Octisalate, 5.0%

Octocrylene, 4.0%

Purpose

Sunscreen

Uses

- Helps prevent sunburn
- If used as directed with other sun protection measures (see Directions), decreases the risk of skin cancer and early skin aging caused by the sun

Warnings

For external use only.

Do not use on

- damaged or broken skin

When using this product

- keep out of eyes. Rinse with water to remove.

Stop use and ask a doctor

- if rash occurs

Keep Out of Reach of Children.

If swallowed, get medical help or contact a Poison Control Center right away.

Directions

- Apply liberally 15 minutes before sun exposure
- Reapply at least every 2 hours
- Use water resistant sunscreen if swimming or sweating
- Children under 6 months of age: ask a doctor
- Sun Protection Measures: Spending time in the sun increases your risk of skin cancer and early skin aging. To decrease this risk, regularly use a sunscreen with a Broad Spectrum SPF value of 15 or higher and other sun protection measures including:
  - Limit time in the sun, especially from 10 a.m. – 2 p.m.
  - Wear long-sleeved shirts, pants, hats and sunglasses

Other Information

- protect the product in this container from excessive heat and direct sun

Inactive ingredients

water, cyclopentasiloxane, C12-15 alkyl benzoate, glyceryl stearate, PEG-100 stearate, steareth-2, polyacrylamide, C13-14 isoparaffin, laureth-7, arachidyl alcohol, behenyl alcohol, arachidyl glucoside, cetearyl alcohol, cetearyl glucoside, steareth-21, glycerin, cetearyl alcohol, phenoxyethanol, triethylene glycol, polymethyl methacrylate, silica, lecithin, soy isoflavones, polysorbate 80, sodium lactate, porphyra umbilicalis extract, panthenol (pro-vitamin B5), opuntia streptacantha stem extract, butyrospermum parkii (shea butter), fragrance, olea europaea (olive) leaf extract, disodium EDTA, olea europaea (olive) fruit oil, simmondsia chinensis (jojoba) seed oil, lavendula angustifolia (lavender) oil, aloe barbadensis leaf juice, benzalkonium chloride, BHT, maris sal (dead sea mineral water), triethanolamine.

Principal Display Panel

nutritious
olive leaf daily defense
broad spectrum SPF 15
sunscreen

DESERT
FUSION™
sea | earth | botanicals

featuring
Aquaguard
Skin Marvel™

quench+protect
paraben-free

1.7 FL OZ (50 mL)

nutritious olive leaf daily defense
broad spectrum SPF 15 sunscreen

Olive leaf has been used for centuries as a medicinal plant due to its high concentration of antioxidants and phytonutrients. Desert Fusion’s Nutritious Olive Leaf Daily Defense Broad Spectrum SPF 15 Sunscreen harnesses the power of the olive to neutralize damaging free radicals and protect skin from irritants. The natural botanicals helps hydrate and nourish the skin throughout the day for healthier, radiant looking skin.

Directions: Apply every morning to clean skin for a healthier looking complexion and to fight the signs of aging.

Visit us at www.desertfusionskincare.com

Made and Exclusively Crafted in Israel

Distributed by:
Emilia Personal Care
5890 Sawmill Road
Suite 230
Dublin, OH 43017

WD629

Carton Label